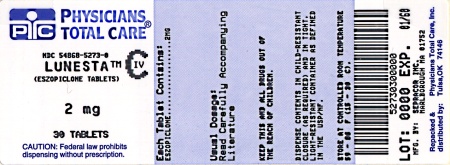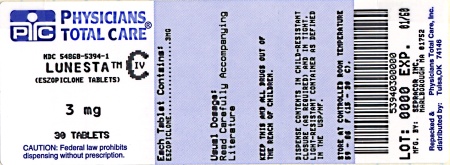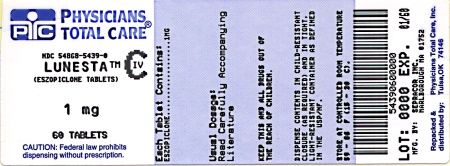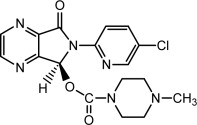 DRUG LABEL: Lunesta
NDC: 54868-5439 | Form: TABLET, COATED
Manufacturer: Physicians Total Care, Inc.
Category: prescription | Type: HUMAN PRESCRIPTION DRUG LABEL
Date: 20120418
DEA Schedule: CIV

ACTIVE INGREDIENTS: ESZOPICLONE 1 mg/1 1
INACTIVE INGREDIENTS: CALCIUM PHOSPHATE, DIBASIC, ANHYDROUS; SILICON DIOXIDE; CROSCARMELLOSE SODIUM; HYPROMELLOSE 2910 (6 MPA.S); LACTOSE MONOHYDRATE; MAGNESIUM STEARATE; CELLULOSE, MICROCRYSTALLINE; POLYETHYLENE GLYCOLS; TITANIUM DIOXIDE; TRIACETIN; FD&C BLUE NO. 2

LUNESTA® (eszopiclone) TABLETS
1 mg, 2 mg, 3 mg

Rx only
C-IV

DESCRIPTION:

LUNESTA (eszopiclone) is a nonbenzodiazepine hypnotic agent that is a pyrrolopyrazine derivative of the cyclopyrrolone class. The chemical name of eszopiclone is (+)-(5S)-6-(5-chloropyridin-2-yl)-7-oxo-6,7-dihydro-5H-pyrrolo[3,4-b] pyrazin-5-yl 4-methylpiperazine-1-carboxylate. Its molecular weight is 388.81, and its empirical formula is C17H17ClN6O3. Eszopiclone has a single chiral center with an (S)-configuration. It has the following chemical structure:

Eszopiclone is a white to light-yellow crystalline solid. Eszopiclone is very slightly soluble in water, slightly soluble in ethanol, and soluble in phosphate buffer (pH 3.2).

Eszopiclone is formulated as film-coated tablets for oral administration. LUNESTA tablets contain 1 mg, 2 mg, or 3 mg eszopiclone and the following inactive ingredients: calcium phosphate, colloidal silicon dioxide, croscarmellose sodium, hypromellose, lactose, magnesium stearate, microcrystalline cellulose, polyethylene glycol, titanium dioxide, and triacetin. In addition, both the 1 mg and 3 mg tablets contain FD&C Blue #2.

CLINICAL PHARMACOLOGY:

Pharmacodynamics

The precise mechanism of action of eszopiclone as a hypnotic is unknown, but its effect is believed to result from its interaction with GABA-receptor complexes at binding domains located close to or allosterically coupled to benzodiazepine receptors. Eszopiclone is a nonbenzodiazepine hypnotic that is a pyrrolopyrazine derivative of the cyclopyrrolone class with a chemical structure unrelated to pyrazolopyrimidines, imidazopyridines, benzodiazepines, barbiturates, or other drugs with known hypnotic properties.

Pharmacokinetics

The pharmacokinetics of eszopiclone have been investigated in healthy subjects (adult and elderly) and in patients with hepatic disease or renal disease. In healthy subjects, the pharmacokinetic profile was examined after single doses of up to 7.5 mg and after once-daily administration of 1, 3, and 6 mg for 7 days. Eszopiclone is rapidly absorbed, with a time to peak concentration (tmax) of approximately 1 hour and a terminal-phase elimination half-life (t1/2) of approximately 6 hours. In healthy adults, LUNESTA does not accumulate with once-daily administration, and its exposure is dose-proportional over the range of 1 to 6 mg.

Absorption And Distribution

Eszopiclone is rapidly absorbed following oral administration. Peak plasma concentrations are achieved within approximately 1 hour after oral administration. Eszopiclone is weakly bound to plasma protein (52-59%). The large free fraction suggests that eszopiclone disposition should not be affected by drug-drug interactions caused by protein binding. The blood-to-plasma ratio for eszopiclone is less than one, indicating no selective uptake by red blood cells.

Metabolism

Following oral administration, eszopiclone is extensively metabolized by oxidation and demethylation. The primary plasma metabolites are (S)-zopiclone-N-oxide and (S)-N-desmethyl zopiclone; the latter compound binds to GABA receptors with substantially lower potency than eszopiclone, and the former compound shows no significant binding to this receptor. In vitro studies have shown that CYP3A4 and CYP2E1 enzymes are involved in the metabolism of eszopiclone. Eszopiclone did not show any inhibitory potential on CYP450 1A2, 2A6, 2C9, 2C19, 2D6, 2E1, and 3A4 in cryopreserved human hepatocytes.

Elimination

After oral administration, eszopiclone is eliminated with a mean t1/2 of approximately 6 hours. Up to 75% of an oral dose of racemic zopiclone is excreted in the urine, primarily as metabolites. A similar excretion profile would be expected for eszopiclone, the S-isomer of racemic zopiclone. Less than 10% of the orally administered eszopiclone dose is excreted in the urine as parent drug.

Effect Of Food

In healthy adults, administration of a 3 mg dose of eszopiclone after a high-fat meal resulted in no change in AUC, a reduction in mean Cmax of 21%, and delayed tmax by approximately 1 hour. The half-life remained unchanged, approximately 6 hours. The effects of LUNESTA on sleep onset may be reduced if it is taken with or immediately after a high-fat/heavy meal.

Special Populations

Age

Compared with non-elderly adults, subjects 65 years and older had an increase of 41% in total exposure (AUC) and a slightly prolonged elimination of eszopiclone (t1/2 approximately 9 hours). Cmax was unchanged. Therefore, in elderly patients the starting dose of LUNESTA should be decreased to 1 mg and the dose should not exceed 2 mg.

Gender

The pharmacokinetics of eszopiclone in men and women are similar.

Race

In an analysis of data on all subjects participating in Phase 1 studies of eszopiclone, the pharmacokinetics for all races studied appeared similar.

Hepatic Impairment

Pharmacokinetics of a 2 mg eszopiclone dose were assessed in 16 healthy volunteers and in 8 subjects with mild, moderate, and severe liver disease. Exposure was increased 2-fold in severely impaired patients compared with the healthy volunteers. Cmax and tmax were unchanged. The dose of LUNESTA should not be increased above 2 mg in patients with severe hepatic impairment. No dose adjustment is necessary for patients with mild-to-moderate hepatic impairment. LUNESTA should be used with caution in patients with hepatic impairment. (See DOSAGE AND ADMINISTRATION.)

Renal Impairment

The pharmacokinetics of eszopiclone were studied in 24 patients with mild, moderate, or severe renal impairment. AUC and Cmax were similar in the patients compared with demographically matched healthy control subjects. No dose adjustment is necessary in patients with renal impairment, since less than 10% of the orally administered eszopiclone dose is excreted in the urine as parent drug.

Drug Interactions

Eszopiclone is metabolized by CYP3A4 and CYP2E1 via demethylation and oxidation. There were no pharmacokinetic or pharmacodynamic interactions between eszopiclone and paroxetine, digoxin, or warfarin. When eszopiclone was coadministered with olanzapine, no pharmacokinetic interaction was detected in levels of eszopiclone or olanzapine, but a pharmacodynamic interaction was seen on a measure of psychomotor function. Eszopiclone and lorazepam decreased each other's Cmax by 22%. Coadministration of eszopiclone 3 mg to subjects receiving ketoconazole 400 mg, a potent inhibitor of CYP3A4, resulted in a 2.2-fold increase in exposure to eszopiclone. LUNESTA would not be expected to alter the clearance of drugs metabolized by common CYP450 enzymes. (See PRECAUTIONS.)

CLINICAL TRIALS:

The effect of LUNESTA on reducing sleep latency and improving sleep maintenance was established in studies with 2100 subjects (ages 18-86) with chronic and transient insomnia in six placebo-controlled trials of up to 6 months' duration. Two of these trials were in elderly patients (n=523). Overall, at the recommended adult dose (2-3 mg) and elderly dose (1-2 mg), LUNESTA significantly decreased sleep latency and improved measures of sleep maintenance (objectively measured as wake time after sleep onset [WASO] and subjectively measured as total sleep time).

Transient Insomnia

Healthy adults were evaluated in a model of transient insomnia (n=436) in a sleep laboratory in a double-blind, parallel-group, single-night trial comparing two doses of eszopiclone and placebo. LUNESTA 3 mg was superior to placebo on measures of sleep latency and sleep maintenance, including polysomnographic (PSG) parameters of latency to persistent sleep (LPS) and WASO.

Chronic Insomnia (Adults And Elderly)

The effectiveness of LUNESTA was established in five controlled studies in chronic insomnia. Three controlled studies were in adult subjects, and two controlled studies were in elderly subjects with chronic insomnia.

Adults

In the first study, adults with chronic insomnia (n=308) were evaluated in a double-blind, parallel-group trial of 6 weeks' duration comparing LUNESTA 2 mg and 3 mg with placebo. Objective endpoints were measured for 4 weeks. Both 2 mg and 3 mg were superior to placebo on LPS at 4 weeks. The 3 mg dose was superior to placebo on WASO.

In the second study, adults with chronic insomnia (n=788) were evaluated using subjective measures in a double-blind, parallel-group trial comparing the safety and efficacy of LUNESTA 3 mg with placebo administered nightly for 6 months. LUNESTA was superior to placebo on subjective measures of sleep latency, total sleep time, and WASO.

In addition, a 6-period cross-over PSG study evaluating eszopiclone doses of 1 to 3 mg, each given over a 2-day period, demonstrated effectiveness of all doses on LPS, and of 3 mg on WASO. In this trial, the response was dose-related.

Elderly

Elderly subjects (ages 65-86) with chronic insomnia were evaluated in two double-blind, parallel-group trials of 2 weeks' duration. One study (n=231) compared the effects of LUNESTA with placebo on subjective outcome measures, and the other (n=292) on objective and subjective outcome measures. The first study compared 1 mg and 2 mg of LUNESTA with placebo, while the second study compared 2 mg of LUNESTA with placebo. All doses were superior to placebo on measures of sleep latency. In both studies, 2 mg of LUNESTA was superior to placebo on measures of sleep maintenance.

Studies Pertinent To Safety Concerns For Sedative/Hypnotic Drugs

Cognitive, Memory, Sedative, and Psychomotor Effects

In two double-blind, placebo-controlled, single-dose cross-over studies of 12 patients each (one study in patients with insomnia; one in normal volunteers), the effects of LUNESTA 2 and 3 mg were assessed on 20 measures of cognitive function and memory at 9.5 and 12 hours after a nighttime dose. Although results suggested that patients receiving LUNESTA 3 mg performed more poorly than patients receiving placebo on a very small number of these measures at 9.5 hours post-dose, no consistent pattern of abnormalities was seen.

In a 6-month double-blind, placebo-controlled trial of nightly administered LUNESTA 3 mg, 8/593 subjects treated with LUNESTA 3 mg (1.3%) and 0/195 subjects treated with placebo (0%) spontaneously reported memory impairment. The majority of these events were mild in nature (5/8), and none were reported as severe. Four of these events occurred within the first 7 days of treatment and did not recur. The incidence of spontaneously reported confusion in this 6-month study was 0.5% in both treatment arms. In a 6-week adult study of nightly administered LUNESTA 2 mg or 3 mg or placebo, the spontaneous reporting rates for confusion were 0%, 3.0%, and 0%, respectively, and for memory impairment were 1%, 1%, and 0%, respectively.

In a 2-week study of 264 elderly insomniacs randomized to either nightly LUNESTA 2 mg or placebo, spontaneous reporting rates of confusion and memory impairment were 0% vs. 0.8% and 1.5% vs. 0%, respectively. In another 2-week study of 231 elderly insomniacs, the spontaneous reporting rates for the 1 mg, 2 mg, and placebo groups for confusion were 0%, 2.5%, and 0%, respectively, and for memory impairment were 1.4%, 0%, and 0%, respectively.

A study of normal subjects exposed to single fixed doses of LUNESTA from 1 to 7.5 mg using the DSST to assess sedation and psychomotor function at fixed times after dosing (hourly up to 16 hours) found the expected sedation and reduction in psychomotor function. This was maximal at 1 hour and present up to 4 hours, but was no longer present by 5 hours.

In another study, patients with insomnia were given 2 or 3 mg doses of LUNESTA nightly, with DSST assessed on the mornings following days 1, 15, and 29 of treatment. While both the placebo and LUNESTA 3 mg groups showed an improvement in DSST scores relative to baseline the following morning (presumably due to a learning effect), the improvement in the placebo group was greater and reached statistical significance on night 1, although not on nights 15 and 29. For the LUNESTA 2 mg group, DSST change scores were not significantly different from placebo at any time point.

Withdrawal-Emergent Anxiety And Insomnia

During nightly use for an extended period, pharmacodynamic tolerance or adaptation has been observed with other hypnotics. If a drug has a short elimination half-life, it is possible that a relative deficiency of the drug or its active metabolites (i.e., in relationship to the receptor site) may occur at some point in the interval between each night's use. This is believed to be responsible for two clinical findings reported to occur after several weeks of nightly use of other rapidly eliminated hypnotics: increased wakefulness during the last quarter of the night and the appearance of increased signs of daytime anxiety.

In a 6-month double-blind, placebo-controlled study of nightly administration of LUNESTA 3 mg, rates of anxiety reported as an adverse event were 2.1% in the placebo arm and 3.7% in the LUNESTA arm. In a 6-week adult study of nightly administration, anxiety was reported as an adverse event in 0%, 2.9%, and 1.0% of the placebo, 2 mg, and 3 mg treatment arms, respectively. In this study, single-blind placebo was administered on nights 45 and 46, the first and second days of withdrawal from study drug. New adverse events were recorded during the withdrawal period, beginning with day 45, up to 14 days after discontinuation. During this withdrawal period, 105 subjects previously taking nightly LUNESTA 3 mg for 44 nights spontaneously reported anxiety (1%), abnormal dreams (1.9%), hyperesthesia (1%), and neurosis (1%), while none of 99 subjects previously taking placebo reported any of these adverse events during the withdrawal period.

Rebound insomnia, defined as a dose-dependent temporary worsening in sleep parameters (latency, sleep efficiency, and number of awakenings) compared with baseline following discontinuation of treatment, is observed with short- and intermediate-acting hypnotics. Rebound insomnia following discontinuation of LUNESTA relative to placebo and baseline was examined objectively in a 6-week adult study on the first 2 nights of discontinuation (nights 45 and 46) following 44 nights of active treatment with 2 mg or 3 mg. In the LUNESTA 2 mg group, compared with baseline, there was a significant increase in WASO and a decrease in sleep efficiency, both occurring only on the first night after discontinuation of treatment. No changes from baseline were noted in the LUNESTA 3 mg group on the first night after discontinuation, and there was a significant improvement in LPS and sleep efficiency compared with baseline following the second night of discontinuation. Comparisons of changes from baseline between LUNESTA and placebo were also performed. On the first night after discontinuation of LUNESTA 2 mg, LPS and WASO were significantly increased and sleep efficiency was reduced; there were no significant differences on the second night. On the first night following discontinuation of LUNESTA 3 mg, sleep efficiency was significantly reduced. No other differences from placebo were noted in any other sleep parameter on either the first or second night following discontinuation. For both doses, the discontinuation-emergent effect was mild, had the characteristics of the return of the symptoms of chronic insomnia, and appeared to resolve by the second night after LUNESTA discontinuation.

INDICATIONS AND USAGE:

LUNESTA is indicated for the treatment of insomnia. In controlled outpatient and sleep laboratory studies, LUNESTA administered at bedtime decreased sleep latency and improved sleep maintenance.

The clinical trials performed in support of efficacy were up to 6 months in duration. The final formal assessments of sleep latency and maintenance were performed at 4 weeks in the 6-week study (adults only), at the end of both 2-week studies (elderly only) and at the end of the 6-month study (adults only).

CONTRAINDICATIONS:

None known.

WARNINGS:

Because sleep disturbances may be the presenting manifestation of a physical and/or psychiatric disorder, symptomatic treatment of insomnia should be initiated only after a careful evaluation of the patient. The failure of insomnia to remit after 7 to 10 days of treatment may indicate the presence of a primary psychiatric and/or medical illness that should be evaluated. Worsening of insomnia or the emergence of new thinking or behavior abnormalities may be the consequence of an unrecognized psychiatric or physical disorder. Such findings have emerged during the course of treatment with sedative/hypnotic drugs, including LUNESTA. Because some of the important adverse effects of LUNESTA appear to be dose-related, it is important to use the lowest possible effective dose, especially in the elderly (see DOSAGE AND ADMINISTRATION).

A variety of abnormal thinking and behavior changes have been reported to occur in association with the use of sedative/hypnotics. Some of these changes may be characterized by decreased inhibition (e.g., aggressiveness and extroversion that seem out of character), similar to effects produced by alcohol and other CNS depressants. Other reported behavioral changes have included bizarre behavior, agitation, hallucinations, and depersonalization. Complex behaviors such as “sleep-driving” (i.e., driving while not fully awake after ingestion of a sedative-hypnotic, with amnesia for the event) have been reported. These events can occur in sedative-hypnotic-naïve as well as in sedative-hypnotic-experienced persons. Although behaviors such as sleep-driving may occur with LUNESTA alone at therapeutic doses, the use of alcohol and other CNS depressants with LUNESTA appears to increase the risk of such behaviors, as does the use of LUNESTA at doses exceeding the maximum recommended dose. Due to the risk to the patient and the community, discontinuation of LUNESTA should be strongly considered for patients who report a “sleep-driving” episode. Other complex behaviors (e.g., preparing and eating food, making phone calls, or having sex) have been reported in patients who are not fully awake after taking a sedative-hypnotic. As with sleep-driving, patients usually do not remember these events. Amnesia and other neuropsychiatric symptoms may occur unpredictably. In primarily depressed patients, worsening of depression, including suicidal thoughts and actions (including completed suicides), have been reported in association with the use of sedative/hypnotics.

It can rarely be determined with certainty whether a particular instance of the abnormal behaviors listed above are drug-induced, spontaneous in origin, or a result of an underlying psychiatric or physical disorder. Nonetheless, the emergence of any new behavioral sign or symptom of concern requires careful and immediate evaluation.

Following rapid dose decrease or abrupt discontinuation of the use of sedative/hypnotics, there have been reports of signs and symptoms similar to those associated with withdrawal from other CNS-depressant drugs (see DRUG ABUSE AND DEPENDENCE).

LUNESTA, like other hypnotics, has CNS-depressant effects. Because of the rapid onset of action, LUNESTA should only be ingested immediately prior to going to bed or after the patient has gone to bed and has experienced difficulty falling asleep. Patients receiving LUNESTA should be cautioned against engaging in hazardous occupations requiring complete mental alertness or motor coordination (e.g., operating machinery or driving a motor vehicle) after ingesting the drug, and be cautioned about potential impairment of the performance of such activities on the day following ingestion of LUNESTA. LUNESTA, like other hypnotics, may produce additive CNS-depressant effects when coadministered with other psychotropic medications, anticonvulsants, antihistamines, ethanol, and other drugs that themselves produce CNS depression. LUNESTA should not be taken with alcohol. Dose adjustment may be necessary when LUNESTA is administered with other CNS-depressant agents, because of the potentially additive effects.

Severe anaphylactic and anaphylactoid reactions

Rare cases of angioedema involving the tongue, glottis or larynx have been reported in patients after taking the first or subsequent doses of sedative-hypnotics, including LUNESTA. Some patients have had additional symptoms such as dyspnea, throat closing, or nausea and vomiting that suggest anaphylaxis. Some patients have required medical therapy in the emergency department. If angioedema involves the tongue, glottis or larynx, airway obstruction may occur and be fatal. Patients who develop angioedema after treatment with LUNESTA should not be rechallenged with the drug.

PRECAUTIONS:

Timing Of Drug Administration

LUNESTA should be taken immediately before bedtime. Taking a sedative/hypnotic while still up and about may result in short-term memory impairment, hallucinations, impaired coordination, dizziness, and lightheadedness.

Use In The Elderly And/Or Debilitated Patients

Impaired motor and/or cognitive performance after repeated exposure or unusual sensitivity to sedative/hypnotic drugs is a concern in the treatment of elderly and/or debilitated patients. The recommended starting dose of LUNESTA for these patients is 1 mg. (See DOSAGE AND ADMINISTRATION.)

Use In Patients With Concomitant Illness

Clinical experience with eszopiclone in patients with concomitant illness is limited. Eszopiclone should be used with caution in patients with diseases or conditions that could affect metabolism or hemodynamic responses.

A study in healthy volunteers did not reveal respiratory-depressant effects at doses 2.5-fold higher (7 mg) than the recommended dose of eszopiclone. Caution is advised, however, if LUNESTA is prescribed to patients with compromised respiratory function.

The dose of LUNESTA should be reduced to 1 mg in patients with severe hepatic impairment, because systemic exposure is doubled in such subjects. No dose adjustment appears necessary for subjects with mild or moderate hepatic impairment. No dose adjustment appears necessary in subjects with any degree of renal impairment, since less than 10% of eszopiclone is excreted unchanged in the urine.

The dose of LUNESTA should be reduced in patients who are administered potent inhibitors of CYP3A4, such as ketoconazole, while taking LUNESTA. Downward dose adjustment is also recommended when LUNESTA is administered with agents having known CNS-depressant effects.

Use In Patients With Depression

Sedative/hypnotic drugs should be administered with caution to patients exhibiting signs and symptoms of depression. Suicidal tendencies may be present in such patients, and protective measures may be required. Intentional overdose is more common in this group of patients; therefore, the least amount of drug that is feasible should be prescribed for the patient at any one time.

Information For Patients

Patients should be instructed to read the accompanying Medication Guide with each new prescription and refill. The complete text of the Medication Guide is reprinted at the end of this document. Patients should be given the following information:

1. Patients should be instructed to take LUNESTA immediately prior to going to bed, and only if they can dedicate 8 hours to sleep.
2. Patients should be instructed not to take LUNESTA with alcohol or with other sedating medications.
3. Patients should be advised to consult with their physician if they have a history of depression, mental illness, or suicidal thoughts, have a history of drug or alcohol abuse, or have liver disease.
4. Women should be advised to contact their physician if they become pregnant, plan to become pregnant, or if they are nursing.

SPECIAL CONCERNS “Sleep-Driving” and other complex behaviors

There have been reports of people getting out of bed after taking a sedative-hypnotic and driving their cars while not fully awake, often with no memory of the event. If a patient experiences such an episode, it should be reported to his or her doctor immediately, since “sleep-driving” can be dangerous. This behavior is more likely to occur when LUNESTA is taken with alcohol or other central nervous system depressants (see WARNINGS). Other complex behaviors (e.g., preparing and eating food, making phone calls, or having sex) have been reported in patients who are not fully awake after taking a sedative-hypnotic. As with sleep-driving, patients usually do not remember these events.

Laboratory Tests

There are no specific laboratory tests recommended.

Drug Interactions

CNS-Active Drugs

Ethanol: An additive effect on psychomotor performance was seen with coadministration of eszopiclone and ethanol 0.70 g/kg for up to 4 hours after ethanol administration.

Paroxetine: Coadministration of single doses of eszopiclone 3 mg and paroxetine 20 mg daily for 7 days produced no pharmacokinetic or pharmacodynamic interaction.

Lorazepam: Coadministration of single doses of eszopiclone 3 mg and lorazepam 2 mg did not have clinically relevant effects on the pharmacodynamics or pharmacokinetics of either drug.

Olanzapine: Coadministration of eszopiclone 3 mg and olanzapine 10 mg produced a decrease in DSST scores. The interaction was pharmacodynamic; there was no alteration in the pharmacokinetics of either drug.

Drugs That Inhibit CYP3A4 (Ketoconazole)

CYP3A4 is a major metabolic pathway for elimination of eszopiclone. The AUC of eszopiclone was increased 2.2-fold by coadministration of ketoconazole, a potent inhibitor of CYP3A4, 400 mg daily for 5 days. Cmax and t1/2 were increased 1.4-fold and 1.3-fold, respectively. Other strong inhibitors of CYP3A4 (e.g., itraconazole, clarithromycin, nefazodone, troleandomycin, ritonavir, nelfinavir) would be expected to behave similarly.

Drugs That Induce CYP3A4 (Rifampicin)

Racemic zopiclone exposure was decreased 80% by concomitant use of rifampicin, a potent inducer of CYP3A4. A similar effect would be expected with eszopiclone.

Drugs Highly Bound To Plasma Protein

Eszopiclone is not highly bound to plasma proteins (52-59% bound); therefore, the disposition of eszopiclone is not expected to be sensitive to alterations in protein binding. Administration of eszopiclone 3 mg to a patient taking another drug that is highly protein-bound would not be expected to cause an alteration in the free concentration of either drug.

Drugs With A Narrow Therapeutic Index

Digoxin: A single dose of eszopiclone 3 mg did not affect the pharmacokinetics of digoxin measured at steady state following dosing of 0.5 mg twice daily for one day and 0.25 mg daily for the next 6 days.

Warfarin: Eszopiclone 3 mg administered daily for 5 days did not affect the pharmacokinetics of (R)- or (S)-warfarin, nor were there any changes in the pharmacodynamic profile (prothrombin time) following a single 25 mg oral dose of warfarin.

Carcinogenesis, Mutagenesis, Impairment Of Fertility

Carcinogenesis

In a carcinogenicity study in Sprague-Dawley rats in which eszopiclone was given by oral gavage, no increases in tumors were seen; plasma levels (AUC) of eszopiclone at the highest dose used in this study (16 mg/kg/day) are estimated to be 80 (females) and 20 (males) times those in humans receiving the maximum recommended human dose (MRHD). However, in a carcinogenicity study in Sprague-Dawley rats in which racemic zopiclone was given in the diet, and in which plasma levels of eszopiclone were reached that were greater than those reached in the above study of eszopiclone, an increase in mammary gland adenocarcinomas in females and an increase in thyroid gland follicular cell adenomas and carcinomas in males were seen at the highest dose of 100 mg/kg/day. Plasma levels of eszopiclone at this dose are estimated to be 150 (females) and 70 (males) times those in humans receiving the MRHD. The mechanism for the increase in mammary adenocarcinomas is unknown. The increase in thyroid tumors is thought to be due to increased levels of TSH secondary to increased metabolism of circulating thyroid hormones, a mechanism that is not considered to be relevant to humans.

In a carcinogenicity study in B6C3F1 mice in which racemic zopiclone was given in the diet, an increase in pulmonary carcinomas and carcinomas plus adenomas in females and an increase in skin fibromas and sarcomas in males were seen at the highest dose of 100 mg/kg/day. Plasma levels of eszopiclone at this dose are estimated to be 8 (females) and 20 (males) times those in humans receiving the MRHD. The skin tumors were due to skin lesions induced by aggressive behavior, a mechanism that is not relevant to humans. A carcinogenicity study was also performed in which CD-1 mice were given eszopiclone at doses up to 100 mg/kg/day by oral gavage; although this study did not reach a maximum tolerated dose, and was thus inadequate for overall assessment of carcinogenic potential, no increases in either pulmonary or skin tumors were seen at doses producing plasma levels of eszopiclone estimated to be 90 times those in humans receiving the MRHD — i.e., 12 times the exposure in the racemate study.

Eszopiclone did not increase tumors in a p53 transgenic mouse bioassay at oral doses up to 300 mg/kg/day.

Mutagenesis

Eszopiclone was positive in the mouse lymphoma chromosomal aberration assay and produced an equivocal response in the Chinese hamster ovary cell chromosomal aberration assay. It was not mutagenic or clastogenic in the bacterial Ames gene mutation assay, in an unscheduled DNA synthesis assay, or in an in vivo mouse bone marrow micronucleus assay.

(S)-N-desmethyl zopiclone, a metabolite of eszopiclone, was positive in the Chinese hamster ovary cell and human lymphocyte chromosomal aberration assays. It was negative in the bacterial Ames mutation assay, in an in vitro ^32P-postlabeling DNA adduct assay, and in an in vivo mouse bone marrow chromosomal aberration and micronucleus assay.

Impairment Of Fertility

Eszopiclone was given by oral gavage to male rats at doses up to 45 mg/kg/day from 4 weeks premating through mating and to female rats at doses up to 180 mg/kg/day from 2 weeks premating through day 7 of pregnancy. An additional study was performed in which only females were treated, up to 180 mg/kg/day. Eszopiclone decreased fertility, probably because of effects in both males and females, with no females becoming pregnant when both males and females were treated with the highest dose; the no-effect dose in both sexes was 5 mg/kg (16 times the MRHD on a mg/m^2 basis). Other effects included increased pre-implantation loss (no-effect dose 25 mg/kg), abnormal estrus cycles (no-effect dose 25 mg/kg), and decreases in sperm number and motility and increases in morphologically abnormal sperm (no-effect dose 5 mg/kg).

Pregnancy

Pregnancy Category C

Eszopiclone administered by oral gavage to pregnant rats and rabbits during the period of organogenesis showed no evidence of teratogenicity up to the highest doses tested (250 and 16 mg/kg/day in rats and rabbits, respectively; these doses are 800 and 100 times, respectively, the maximum recommended human dose [MRHD] on a mg/m^2 basis). In the rat, slight reductions in fetal weight and evidence of developmental delay were seen at maternally toxic doses of 125 and 150 mg/kg/day, but not at 62.5 mg/kg/day (200 times the MRHD on a mg/m^2 basis).

Eszopiclone was also administered by oral gavage to pregnant rats throughout the pregnancy and lactation periods at doses of up to 180 mg/kg/day. Increased post-implantation loss, decreased postnatal pup weights and survival, and increased pup startle response were seen at all doses; the lowest dose tested, 60 mg/kg/day, is 200 times the MRHD on a mg/m^2 basis. These doses did not produce significant maternal toxicity. Eszopiclone had no effects on other behavioral measures or reproductive function in the offspring.

There are no adequate and well-controlled studies of eszopiclone in pregnant women. Eszopiclone should be used during pregnancy only if the potential benefit justifies the potential risk to the fetus.

Labor And Delivery

LUNESTA has no established use in labor and delivery.

Nursing Mothers

It is not known whether LUNESTA is excreted in human milk. Because many drugs are excreted in human milk, caution should be exercised when LUNESTA is administered to a nursing woman.

Pediatric Use

Safety and effectiveness of eszopiclone in children below the age of 18 have not been established.

Geriatric Use

A total of 287 subjects in double-blind, parallel-group, placebo-controlled clinical trials who received eszopiclone were 65 to 86 years of age. The overall pattern of adverse events for elderly subjects (median age = 71 years) in 2-week studies with nighttime dosing of 2 mg eszopiclone was not different from that seen in younger adults (see ADVERSE REACTIONS, Table 2). LUNESTA 2 mg exhibited significant reduction in sleep latency and improvement in sleep maintenance in the elderly population.

ADVERSE REACTIONS:

The premarketing development program for LUNESTA included eszopiclone exposures in patients and/or normal subjects from two different groups of studies: approximately 400 normal subjects in clinical pharmacology/pharmacokinetic studies, and approximately 1550 patients in placebo-controlled clinical effectiveness studies, corresponding to approximately 263 patient-exposure years. The conditions and duration of treatment with LUNESTA varied greatly and included (in overlapping categories) open-label and double-blind phases of studies, inpatients and outpatients, and short-term and longer-term exposure. Adverse reactions were assessed by collecting adverse events, results of physical examinations, vital signs, weights, laboratory analyses, and ECGs.

Adverse events during exposure were obtained primarily by general inquiry and recorded by clinical investigators using terminology of their own choosing. Consequently, it is not possible to provide a meaningful estimate of the proportion of individuals experiencing adverse events without first grouping similar types of events into a smaller number of standardized event categories. In the tables and tabulations that follow, COSTART terminology has been used to classify reported adverse events.

The stated frequencies of adverse events represent the proportion of individuals who experienced, at least once, a treatment-emergent adverse event of the type listed. An event was considered treatment-emergent if it occurred for the first time or worsened while the patient was receiving therapy following baseline evaluation.

Adverse Findings Observed In Placebo-Controlled Trials

Adverse Events Resulting In Discontinuation Of Treatment

In placebo-controlled, parallel-group clinical trials in the elderly, 3.8% of 208 patients who received placebo, 2.3% of 215 patients who received 2 mg LUNESTA, and 1.4% of 72 patients who received 1 mg LUNESTA discontinued treatment due to an adverse event. In the 6-week parallel-group study in adults, no patients in the 3 mg arm discontinued because of an adverse event. In the long-term 6-month study in adult insomnia patients, 7.2% of 195 patients who received placebo and 12.8% of 593 patients who received 3 mg LUNESTA discontinued due to an adverse event. No event that resulted in discontinuation occurred at a rate of greater than 2%.

Adverse Events Observed At An Incidence Of ≥2% In Controlled Trials

Table 1 shows the incidence of treatment-emergent adverse events from a Phase 3 placebo-controlled study of LUNESTA at doses of 2 or 3 mg in non-elderly adults. Treatment duration in this trial was 44 days. The table includes only events that occurred in 2% or more of patients treated with LUNESTA 2 mg or 3 mg in which the incidence in patients treated with LUNESTA was greater than the incidence in placebo-treated patients.

Table 1: Incidence (%) of Treatment-Emergent Adverse Events in a 6-Week Placebo-Controlled Study in Non-Elderly Adults with LUNESTA^1
Adverse Event | Placebo (n=99) | LUNESTA 2 mg (n=104) | LUNESTA 3 mg (n=105)
Body as a Whole
Headache | 13 | 21 | 17
Viral Infection | 1 | 3 | 3
Digestive System
Dry Mouth | 3 | 5 | 7
Dyspepsia | 4 | 4 | 5
Nausea | 4 | 5 | 4
Vomiting | 1 | 3 | 0
Nervous System
Anxiety | 0 | 3 | 1
Confusion | 0 | 0 | 3
Depression | 0 | 4 | 1
Dizziness | 4 | 5 | 7
Hallucinations | 0 | 1 | 3
Libido Decreased | 0 | 0 | 3
Nervousness | 3 | 5 | 0
Somnolence | 3 | 10 | 8
Respiratory System
Infection | 3 | 5 | 10
Skin and Appendages
Rash | 1 | 3 | 4
Special Senses
Unpleasant Taste | 3 | 17 | 34
Urogenital System
Dysmenorrhea * | 0 | 3 | 0
Gynecomastia ** | 0 | 3 | 0
^1 Events for which the LUNESTA incidence was equal to or less than placebo are not listed on the table, but included the following: abnormal dreams, accidental injury, back pain, diarrhea, flu syndrome, myalgia, pain, pharyngitis, and rhinitis.
* Gender-specific adverse event in females
** Gender-specific adverse event in males

Adverse events from Table 1 that suggest a dose-response relationship in adults include viral infection, dry mouth, dizziness, hallucinations, infection, rash, and unpleasant taste, with this relationship clearest for unpleasant taste.

Table 2 shows the incidence of treatment-emergent adverse events from combined Phase 3 placebo-controlled studies of LUNESTA at doses of 1 or 2 mg in elderly adults (ages 65-86). Treatment duration in these trials was 14 days. The table includes only events that occurred in 2% or more of patients treated with LUNESTA 1 mg or 2 mg in which the incidence in patients treated with LUNESTA was greater than the incidence in placebo-treated patients.

Table 2: Incidence (%) of Treatment-Emergent Adverse Events in Elderly Adults (Ages 65-86) in 2-Week Placebo-Controlled Trials with LUNESTA^1
Adverse Event | Placebo (n=208) | LUNESTA 1 mg (n=72) | LUNESTA 2 mg (n=215)
Body as a Whole
Accidental Injury | 1 | 0 | 3
Headache | 14 | 15 | 13
Pain | 2 | 4 | 5
Digestive System
Diarrhea | 2 | 4 | 2
Dry Mouth | 2 | 3 | 7
Dyspepsia | 2 | 6 | 2
Nervous System
Abnormal Dreams | 0 | 3 | 1
Dizziness | 2 | 1 | 6
Nervousness | 1 | 0 | 2
Neuralgia | 0 | 3 | 0
Skin and Appendages
Pruritus | 1 | 4 | 1
Special Senses
Unpleasant Taste | 0 | 8 | 12
Urogenital System
Urinary Tract Infection | 0 | 3 | 0
^1 Events for which the LUNESTA incidence was equal to or less than placebo are not listed on the table, but included the following: abdominal pain, asthenia, nausea, rash, and somnolence.

Adverse events from Table 2 that suggest a dose-response relationship in elderly adults include pain, dry mouth, and unpleasant taste, with this relationship again clearest for unpleasant taste.

These figures cannot be used to predict the incidence of adverse events in the course of usual medical practice because patient characteristics and other factors may differ from those that prevailed in the clinical trials. Similarly, the cited frequencies cannot be compared with figures obtained from other clinical investigations involving different treatments, uses, and investigators. The cited figures, however, do provide the prescribing physician with some basis for estimating the relative contributions of drug and non-drug factors to the adverse event incidence rate in the population studied.

Other Events Observed During The Premarketing Evaluation Of LUNESTA

Following is a list of modified COSTART terms that reflect treatment-emergent adverse events as defined in the introduction to the ADVERSE REACTIONS section and reported by approximately 1550 subjects treated with LUNESTA at doses in the range of 1 to 3.5 mg/day during Phase 2 and 3 clinical trials throughout the United States and Canada. All reported events are included except those already listed in Tables 1 and 2 or elsewhere in labeling, minor events common in the general population, and events unlikely to be drug-related. Although the events reported occurred during treatment with LUNESTA, they were not necessarily caused by it.

Events are further categorized by body system and listed in order of decreasing frequency according to the following definitions: frequent adverse events are those that occurred on one or more occasions in at least 1/100 patients; infrequent adverse events are those that occurred in fewer than 1/100 patients but in at least 1/1,000 patients; rare adverse events are those that occurred in fewer than 1/1,000 patients. Gender-specific events are categorized based on their incidence for the appropriate gender.

Body as a Whole: Frequent: chest pain; Infrequent: allergic reaction, cellulitis, face edema, fever, halitosis, heat stroke, hernia, malaise, neck rigidity, photosensitivity.

Cardiovascular System: Frequent: migraine; Infrequent: hypertension; Rare: thrombophlebitis.

Digestive System: Infrequent: anorexia, cholelithiasis, increased appetite, melena, mouth ulceration, thirst, ulcerative stomatitis; Rare: colitis, dysphagia, gastritis, hepatitis, hepatomegaly, liver damage, stomach ulcer, stomatitis, tongue edema, rectal hemorrhage.

Hemic and Lymphatic System: Infrequent: anemia, lymphadenopathy.

Metabolic and Nutritional: Frequent: peripheral edema; Infrequent: hypercholesteremia, weight gain, weight loss; Rare: dehydration, gout, hyperlipemia, hypokalemia.

Musculoskeletal System: Infrequent: arthritis, bursitis, joint disorder (mainly swelling, stiffness, and pain), leg cramps, myasthenia, twitching; Rare: arthrosis, myopathy, ptosis.

Nervous System: Infrequent: agitation, apathy, ataxia, emotional lability, hostility, hypertonia, hypesthesia, incoordination, insomnia, memory impairment, neurosis, nystagmus, paresthesia, reflexes decreased, thinking abnormal (mainly difficulty concentrating), vertigo; Rare: abnormal gait, euphoria, hyperesthesia, hypokinesia, neuritis, neuropathy, stupor, tremor.

Respiratory System: Infrequent: asthma, bronchitis, dyspnea, epistaxis, hiccup, laryngitis.

Skin and Appendages: Infrequent: acne, alopecia, contact dermatitis, dry skin, eczema, skin discoloration, sweating, urticaria; Rare: erythema multiforme, furunculosis, herpes zoster, hirsutism, maculopapular rash, vesiculobullous rash.

Special Senses: Infrequent: conjunctivitis, dry eyes, ear pain, otitis externa, otitis media, tinnitus, vestibular disorder; Rare: hyperacusis, iritis, mydriasis, photophobia.

Urogenital System: Infrequent: amenorrhea, breast engorgement, breast enlargement, breast neoplasm, breast pain, cystitis, dysuria, female lactation, hematuria, kidney calculus, kidney pain, mastitis, menorrhagia, metrorrhagia, urinary frequency, urinary incontinence, uterine hemorrhage, vaginal hemorrhage, vaginitis; Rare: oliguria, pyelonephritis, urethritis.

DRUG ABUSE AND DEPENDENCE:

Controlled Substance Class

LUNESTA is a Schedule IV controlled substance under the Controlled Substances Act. Other substances under the same classification are benzodiazepines and the nonbenzodiazepine hypnotics zaleplon and zolpidem. While eszopiclone is a hypnotic agent with a chemical structure unrelated to benzodiazepines, it shares some of the pharmacologic properties of the benzodiazepines.

Abuse, Dependence, And Tolerance

Abuse And Dependence

Abuse and addiction are separate and distinct from physical dependence and tolerance. Abuse is characterized by misuse of the drug for non-medical purposes, often in combination with other psychoactive substances. Physical dependence is a state of adaptation that is manifested by a specific withdrawal syndrome that can be produced by abrupt cessation, rapid dose reduction, decreasing blood level of the drug and/or administration of an antagonist. Tolerance is a state of adaptation in which exposure to a drug induces changes that result in a diminution of one or more of the drug's effects over time. Tolerance may occur to both the desired and undesired effects of drugs and may develop at different rates for different effects.

Addiction is a primary, chronic, neurobiological disease with genetic, psychosocial, and environmental factors influencing its development and manifestations. It is characterized by behaviors that include one or more of the following: impaired control over drug use, compulsive use, continued use despite harm, and craving. Drug addiction is a treatable disease, utilizing a multidisciplinary approach, but relapse is common.

In a study of abuse liability conducted in individuals with known histories of benzodiazepine abuse, eszopiclone at doses of 6 and 12 mg produced euphoric effects similar to those of diazepam 20 mg. In this study, at doses 2-fold or greater than the maximum recommended doses, a dose-related increase in reports of amnesia and hallucinations was observed for both LUNESTA and diazepam.

The clinical trial experience with LUNESTA revealed no evidence of a serious withdrawal syndrome. Nevertheless, the following adverse events included in DSM-IV criteria for uncomplicated sedative/hypnotic withdrawal were reported during clinical trials following placebo substitution occurring within 48 hours following the last LUNESTA treatment: anxiety, abnormal dreams, nausea, and upset stomach. These reported adverse events occurred at an incidence of 2% or less. Use of benzodiazepines and similar agents may lead to physical and psychological dependence. The risk of abuse and dependence increases with the dose and duration of treatment and concomitant use of other psychoactive drugs. The risk is also greater for patients who have a history of alcohol or drug abuse or history of psychiatric disorders. These patients should be under careful surveillance when receiving LUNESTA or any other hypnotic.

Tolerance

Some loss of efficacy to the hypnotic effect of benzodiazepines and benzodiazepine-like agents may develop after repeated use of these drugs for a few weeks.

No development of tolerance to any parameter of sleep measurement was observed over six months. Tolerance to the efficacy of LUNESTA 3 mg was assessed by 4-week objective and 6-week subjective measurements of time to sleep onset and sleep maintenance for LUNESTA in a placebo-controlled 44-day study, and by subjective assessments of time to sleep onset and WASO in a placebo-controlled study for 6 months.

OVERDOSAGE:

There is limited premarketing clinical experience with the effects of an overdosage of LUNESTA. In clinical trials with eszopiclone, one case of overdose with up to 36 mg of eszopiclone was reported in which the subject fully recovered. Individuals have fully recovered from racemic zopiclone overdoses up to 340 mg (56 times the maximum recommended dose of eszopiclone).

Signs and symptoms of overdose effects of CNS depressants can be expected to present as exaggerations of the pharmacological effects noted in preclinical testing. Impairment of consciousness ranging from somnolence to coma has been described. Rare individual instances of fatal outcomes following overdose with racemic zopiclone have been reported in European postmarketing reports, most often associated with overdose with other CNS-depressant agents.

Recommended Treatment

General symptomatic and supportive measures should be used along with immediate gastric lavage where appropriate. Intravenous fluids should be administered as needed. Flumazenil may be useful. As in all cases of drug overdose, respiration, pulse, blood pressure, and other appropriate signs should be monitored and general supportive measures employed. Hypotension and CNS depression should be monitored and treated by appropriate medical intervention. The value of dialysis in the treatment of overdosage has not been determined.

Poison Control Center

As with the management of all overdosage, the possibility of multiple drug ingestion should be considered. The physician may wish to consider contacting a poison control center for up-to-date information on the management of hypnotic drug product overdosage.

DOSAGE AND ADMINISTRATION:

The dose of LUNESTA should be individualized. The recommended starting dose for LUNESTA for most non-elderly adults is 2 mg immediately before bedtime. Dosing can be initiated at or raised to 3 mg if clinically indicated, since 3 mg is more effective for sleep maintenance (see PRECAUTIONS).

The recommended starting dose of LUNESTA for elderly patients whose primary complaint is difficulty falling asleep is 1 mg immediately before bedtime. In these patients, the dose may be increased to 2 mg if clinically indicated. For elderly patients whose primary complaint is difficulty staying asleep, the recommended dose is 2 mg immediately before bedtime (see PRECAUTIONS).

Taking LUNESTA with or immediately after a heavy, high-fat meal results in slower absorption and would be expected to reduce the effect of LUNESTA on sleep latency (see Pharmacokinetics under CLINICAL PHARMACOLOGY).

Special Populations

Hepatic

The starting dose of LUNESTA should be 1 mg in patients with severe hepatic impairment. LUNESTA should be used with caution in these patients.

Coadministration With CYP3A4 Inhibitors

The starting dose of LUNESTA should not exceed 1 mg in patients coadministered LUNESTA with potent CYP3A4 inhibitors. If needed, the dose can be raised to 2 mg.

HOW SUPPLIED:

LUNESTA 3 mg tablets are round, dark blue, film-coated, and identified with debossed markings of S193 on one side, and are supplied as:

Bottles of 10 | NDC 54868-5394-0
Bottles of 15 | NDC 54868-5394-2
Bottles of 30 | NDC 54868-5394-1
Bottles of 90 | NDC 54868-5394-3

LUNESTA 2 mg tablets are round, white, film-coated, and identified with debossed markings of S191 on one side, and are supplied as:

Bottles of 10 | NDC 54868-5273-1
Bottles of 20 | NDC 54868-5273-2
Bottles of 30 | NDC 54868-5273-0

LUNESTA 1 mg tablets are round, light blue, film-coated, and identified with debossed markings of S190 on one side, and are supplied as:

Bottles of 20 | NDC 54868-5439-1
Bottles of 60 | NDC 54868-5439-0

STORAGE AND HANDLING

Store at 25°C (77°F); excursions permitted to 15°C to 30°C (59°F to 86°F) [see USP Controlled Room Temperature].

SUNOVION

Manufactured for:
Sunovion Pharmaceuticals Inc.
Marlborough, MA 01752 USA

For customer service, call 1-888-394-7377.
To report adverse events, call 1-877-737-7226.
For medical information, call 1-800-739-0565.

© 2009, 2010 Sunovion Pharmaceuticals Inc. All rights reserved.
Lunesta is a registered trademark of Sunovion Pharmaceuticals Inc.

Relabeling and Repackaging by:
Physicians Total Care, Inc.
Tulsa, Oklahoma 74146

MEDICATION GUIDE

LUNESTA® (lū'-nes''-tă) Tablets, Coated C-IV
(eszopiclone)

Read the Medication Guide that comes with LUNESTA before you start taking it and each time you get a refill. There may be new information. This Medication Guide does not take the place of talking to your doctor about your medical condition or treatment.

What is the most important information I should know about LUNESTA?

After taking LUNESTA, you may get up out of bed while not being fully awake and do an activity that you do not know you are doing. The next morning, you may not remember that you did anything during the night. You have a higher chance for doing these activities if you drink alcohol or take other medicines that make you sleepy with LUNESTA. Reported activities include:

- driving a car ("sleep-driving")
- making and eating food
- talking on the phone
- having sex
- sleep-walking

Call your doctor right away if you find out that you have done any of the above activities after taking LUNESTA.

Important:

1. Take LUNESTA exactly as prescribed
  - Do not take more LUNESTA than prescribed.
  - Take LUNESTA right before you get in bed, not sooner.
2. Do not take LUNESTA if you:
  - drink alcohol
  - take other medicines that can make you sleepy. Talk to your doctor about all of your medicines. Your doctor will tell you if you can take LUNESTA with your other medicines
  - cannot get a full night's sleep

WHAT IS LUNESTA?

LUNESTA is a sedative-hypnotic (sleep) medicine. LUNESTA is used in adults for the treatment of a sleep problem called insomnia. Symptoms of insomnia include:

- trouble falling asleep
- waking up often during the night

LUNESTA is not for children.

LUNESTA is a federally controlled substance (C-IV) because it can be abused or lead to dependence. Keep LUNESTA in a safe place to prevent misuse and abuse. Selling or giving away LUNESTA may harm others, and is against the law. Tell your doctor if you have ever abused or been dependent on alcohol, prescription medicines or street drugs.

Who should not take LUNESTA?

Do not take LUNESTA if you are allergic to anything in it.

See the end of this Medication Guide for a complete list of ingredients in LUNESTA.

LUNESTA may not be right for you. Before starting LUNESTA, tell your doctor about all of your health conditions, including if you:

- have a history of depression, mental illness, or suicidal thoughts
- have a history of drug or alcohol abuse or addiction
- have liver disease
- are pregnant, planning to become pregnant, or breastfeeding

Tell your doctor about all of the medicines you take including prescription and nonprescription medicines, vitamins and herbal supplements. Medicines can interact with each other, sometimes causing serious side effects. Do not take LUNESTA with other medicines that can make you sleepy.

Know the medicines you take. Keep a list of your medicines with you to show your doctor and pharmacist each time you get a new medicine.

How should I take LUNESTA?

- Take LUNESTA exactly as prescribed. Do not take more LUNESTA than prescribed for you.
- Take LUNESTA right before you get into bed.
- Do not take LUNESTA with or right after a meal.
- Do not take LUNESTA unless you are able to get a full night's sleep before you must be active again.
- Call your doctor if your insomnia worsens or is not better within 7 to 10 days. This may mean that there is another condition causing your sleep problems.
- If you take too much LUNESTA or overdose, call your doctor or poison control center right away, or get emergency treatment.

What are the possible side effects of LUNESTA?

Possible serious side effects of LUNESTA include:

- getting out of bed while not being fully awake and do an activity that you do not know you are doing. (See “What is the most important information I should know about LUNESTA?)
- abnormal thoughts and behavior. Symptoms include more outgoing or aggressive behavior than normal, confusion, agitation, hallucinations, worsening of depression, and suicidal thoughts or actions.
- memory loss
- anxiety
- severe allergic reactions. Symptoms include swelling of the tongue or throat, trouble breathing, and nausea and vomiting. Get emergency medical help if you get these symptoms after taking LUNESTA.

Call your doctor right away if you have any of the above side effects or any other side effects that worry you while using LUNESTA.

The most common side effects of LUNESTA are:

- unpleasant taste in mouth, dry mouth
- drowsiness
- dizziness
- headache
- symptoms of the common cold
- You may still feel drowsy the next day after taking LUNESTA. Do not drive or do other dangerous activities after taking LUNESTA until you feel fully awake.

These are not all the side effects of LUNESTA. Ask your doctor or pharmacist for more information. Call your doctor for medical advice about side effects. You may report side effects to FDA at 1-800-FDA-1088.

How should I Store LUNESTA?

- Store LUNESTA at room temperature, between 59°F to 86°F (15°C to 30°C).
- Do not use LUNESTA after the expiration date.
- Keep LUNESTA and all medicines out of reach of children.

General Information about LUNESTA

- Medicines are sometimes prescribed for purposes other than those listed in a Medication Guide.
- Do not use LUNESTA for a condition for which it was not prescribed.
- Do not share LUNESTA with other people, even if you think they have the same symptoms that you have. It may harm them and is against the law.

This Medication Guide summarizes the most important information about LUNESTA. If you would like more information, talk with your doctor. You can ask your doctor or pharmacist for information about LUNESTA that is written for healthcare professionals.

- For customer service, call 1-888-394-7377.
- To report side effects, call 1-877-737-7226.
- For medical information, call 1-800-739-0565.

What are the ingredients in LUNESTA?

Active Ingredient: eszopiclone.

Inactive Ingredients: calcium phosphate, colloidal silicon dioxide, croscarmellose sodium, hypromellose, lactose, magnesium stearate, microcrystalline cellulose, polyethylene glycol, titanium dioxide, and triacetin.

Rx Only

This Medication Guide has been approved by the U.S. Food and Drug Administration.

SUNOVION

Manufactured for:
Sunovion Pharmaceuticals Inc.
Marlborough, MA 01752 USA

© 2009, 2010 Sunovion Pharmaceuticals Inc. All rights reserved.
Lunesta is a registered trademark of Sunovion Pharmaceuticals Inc.

November 2010
901031R06

1 MG BOTTLE LABEL – PRINCIPAL DISPLAY PANEL – 1mg

Lunesta®

(eszopiclone) Tablets

1 mg C-IV

DISPENSER: Each time Lunesta is

dispensed give the patient a medication

guide, also provided at www.Lunesta.com

or 1-888-394-7377.

Rx Only

2 MG BOTTLE LABEL – PRINCIPAL DISPLAY PANEL – 2mg

Lunesta®

(eszopiclone) Tablets

2 mg C-IV

DISPENSER: Each time Lunesta is

dispensed give the patient a medication

guide, also provided at www.Lunesta.com

or 1-888-394-7377.

Rx Only

3 MG BOTTLE LABEL – PRINCIPAL DISPLAY PANEL – 3mg

Lunesta®

(eszopiclone) Tablets

3 mg C-IV

DISPENSER: Each time Lunesta is

dispensed give the patient a medication

guide, also provided at www.Lunesta.com

or 1-888-394-7377.

Rx Only